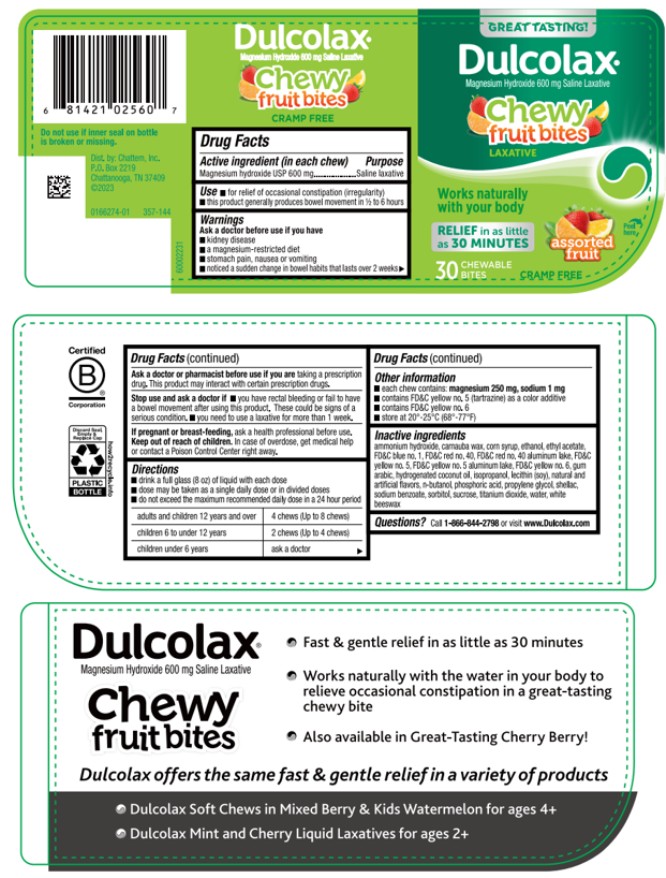 DRUG LABEL: Dulcolax Chewy Bites Assorted Fruits
NDC: 41167-0256 | Form: TABLET, CHEWABLE
Manufacturer: Chattem, Inc.
Category: otc | Type: HUMAN OTC DRUG LABEL
Date: 20260114

ACTIVE INGREDIENTS: MAGNESIUM HYDROXIDE 600 mg/1 1
INACTIVE INGREDIENTS: AMMONIA; CARNAUBA WAX; CORN SYRUP; ALCOHOL; ETHYL ACETATE; FD&C BLUE NO. 1; ACACIA; FD&C YELLOW NO. 5; FD&C YELLOW NO. 5 ALUMINUM LAKE; FD&C YELLOW NO. 6; HYDROGENATED COCONUT OIL; ISOPROPYL ALCOHOL; LECITHIN, SOYBEAN; BUTYL ALCOHOL; PHOSPHORIC ACID; PROPYLENE GLYCOL; SHELLAC; SODIUM BENZOATE; SORBITOL; SUCROSE; TITANIUM DIOXIDE; WATER; WHITE WAX; FD&C RED NO. 40

Dulcolax Chewy Fruit Bites-Assorted Fruits

Dulcolax Chewy Fruit Bites Saline Laxative

Drug Facts

Active ingredient (in each chew)

Magnesium hydroxide USP 600 mg

Purpose

Saline laxative

Use

● for relief of occasional constipation (irregularity)

● this product generally produces bowel movement in ½ to 6 hours

Warnings

Ask a doctor before use if you have

● kidney disease

● a magnesium-restricted diet

● stomach pain, nausea or vomiting

● noticed a sudden change in bowel habits that lasts over 2 weeks

Ask a doctor or pharmacist before use if you are

taking a prescription drug. This product may interact with certain prescription drugs.

Stop use and ask a doctor if

● you have rectal bleeding or fail to have a bowel movement after using this product. These could be signs of a serious condition.

● you need to use a laxative for more than 1 week.

If pregnant or breast-feeding,

ask a health professional before use.

Keep out of reach of children.

In case of overdose, get medical help or contact a Poison Control Center right away.

Directions

● drink a full glass (8 oz) of liquid with each dose

● dose may be taken as a single daily dose or in divided doses

● do not exceed the maximum recommended daily dose in a 24 hour period

adults and children 12 years and over | 4 chews (Up to 8 chews)
children 6 to under 12 years | 2 chews (Up to 4 chews)
children under 6 years | ask a doctor

Other information

● each chew contains: magnesium 250 mg, sodium 1 mg

● contains FD&C yellow no. 5 (tartrazine) as a color additive

● contains FD&C yellow no. 6

● store at 20°-25°C (68°-77°F)

Inactive ingredients

ammonium hydroxide, carnauba wax, corn syrup, ethanol, ethyl acetate, FD&C blue no. 1, FD&C red no. 40, FD&C red no. 40 aluminum lake, FD&C yellow no. 5, FD&C yellow no. 5 aluminum lake, FD&C yellow no. 6, gum arabic, hydrogenated coconut oil, isopropanol, lecithin (soy), natural and artificial flavors, n-butanol, phosphoric acid, propylene glycol, shellac, sodium benzoate, sorbitol, sucrose, titanium dioxide, water, white beeswax

Questions?

Call 1-866-844-2798 or visit www.Dulcolax.com

PRINCIPAL DISPLAY PANEL

Dulcolax
Magnesium Hydroxide 600 mg Saline Laxative
Chewy fruit bites
assorted fruit
30 CHEWABLE BITES